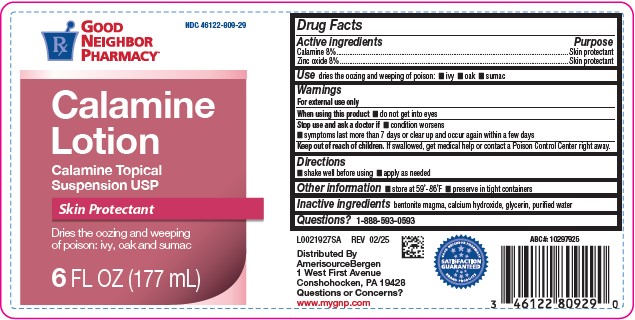 DRUG LABEL: Calamine
NDC: 46122-809 | Form: LOTION
Manufacturer: AMERISOURCE BERGEN
Category: otc | Type: HUMAN OTC DRUG LABEL
Date: 20260129

ACTIVE INGREDIENTS: FERRIC OXIDE RED 80 mg/100 mL; ZINC OXIDE 80 mg/100 mL
INACTIVE INGREDIENTS: GLYCERIN; CALCIUM HYDROXIDE; BENTONITE; WATER

Good Neighbor Pharmacy 063.001/063AA
Calamine Lotion

Active ingredients

Calamine 8%
Zinc oxide 8%

Purpose

Skin protectant

Uses

dries the oozing and weeping of poison:

- ivy
- oak
- sumac

Warnings

For external use only

When using this product

- do not get into eyes

Stop use and ask a doctor if

- condition worsens
- symptoms last more than 7 days or clear up and occur again within a few days

Keep out of reach of children.

If swallowed, get medical help or contact a Poison Control Center right away.

Directions

- shake well before using
- apply as needed

Other information

- store at 59° - 86°F
- Preserve in tight containers

Inactive ingredients

bentonite magma, calcium hydroxide, glycerin, purified water

Questions?

1-888-593-0593

ADVERSE REACTION

Distributed By

AmerisourceBergen

1 West First Avenue

Conshohocken, PA 19428

Questions or Concerns?

www.mygnp.com

SATISFACTION GUARANTEED

GOOD NEIGHBOR PHARMACY BRAND PRODUCTS

PRINCIPAL DISPLAY PANEL

NDC 46122-809-29

GOOD NEIGHBOR PHARMACY®

Calamine Lotion

Calamine Topical Suspension USP

Skin Protectant

Dries the oozing and weeping of poison: ivy, oak and sumac

6 FL OZ (177 mL)